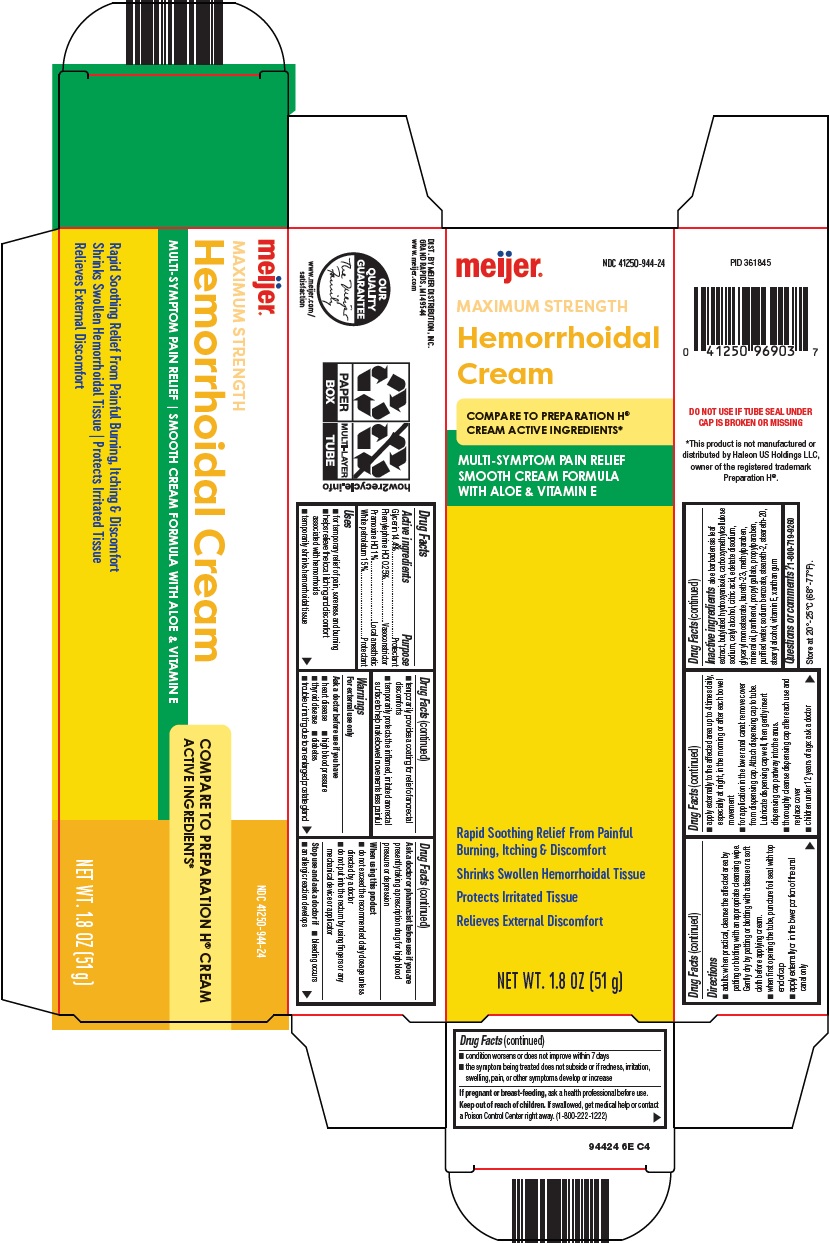 DRUG LABEL: hemorrhoidal
NDC: 41250-944 | Form: CREAM
Manufacturer: Meijer Distribution Inc
Category: otc | Type: HUMAN OTC DRUG LABEL
Date: 20241015

ACTIVE INGREDIENTS: GLYCERIN 14.4 g/100 g; PHENYLEPHRINE HYDROCHLORIDE 0.25 g/100 g; PRAMOXINE HYDROCHLORIDE 1 g/100 g; PETROLATUM 15 g/100 g
INACTIVE INGREDIENTS: ALOE VERA LEAF; BUTYLATED HYDROXYANISOLE; CARBOXYMETHYLCELLULOSE SODIUM, UNSPECIFIED; CETYL ALCOHOL; CITRIC ACID MONOHYDRATE; EDETATE DISODIUM; GLYCERYL MONOSTEARATE; LAURETH-23; METHYLPARABEN; MINERAL OIL; PANTHENOL; PROPYL GALLATE; PROPYLPARABEN; WATER; SODIUM BENZOATE; STEARETH-2; STEARETH-20; STEARYL ALCOHOL; .ALPHA.-TOCOPHEROL; XANTHAN GUM

Meijer Distribution, Inc. Hemorrhoidal Cream Drug Facts

Active ingredients

Glycerin 14.4%

Phenylephrine HCl 0.25%

Pramoxine HCl 1%

White petrolatum 15%

Purpose

Protectant

Vasoconstrictor

Local anesthetic

Uses

1. for temporary relief of pain, soreness and burning
2. helps relieve the local itching and discomfort associated with hemorrhoids
3. temporarily shrinks hemorrhoidal tissue
4. temporarily provides a coating for relief of anorectal discomforts
5. temporarily protects the inflamed, irritated anorectal surface to help make bowel movements less painful

Warnings

For external use only

Ask a doctor before use if you have

1. heart disease
2. high blood pressure
3. thyroid disease
4. diabetes
5. trouble urinating due to an enlarged prostate gland

Ask a doctor or pharmacist before use if you are

presently taking a prescription drug for high blood pressure or depression

When using this product

1. do not exceed the recommended daily dosage unless directed by a doctor
2. do not put into the rectum by using fingers or any mechanical device or applicator

Stop use and ask a doctor if

1. bleeding occurs
2. condition worsens or does not improve within 7 days
3. an allergic reaction develops
4. the symptom being treated does not subside or if redness, irritation, swelling, pain, or other symptoms develop or increase

If pregnant or breast-feeding,

ask a health professional before use.

Keep out of reach of children.

If swallowed, get medical help or contact a Poison Control Center right away. (1-800-222-1222)

Directions

1. adults: when practical, cleanse the affected area by patting or blotting with an appropriate cleansing wipe. Gently dry by patting or blotting with a tissue or a soft cloth before applying cream.
2. when first opening the tube, puncture foil seal with top end of cap
3. apply externally or in the lower portion of the anal canal only
4. apply externally to the affected area up to 4 times daily, especially at night, in the morning or after each bowel movement
5. for application in the lower anal canal: remove cover from dispensing cap. Attach dispensing cap to tube. Lubricate dispensing cap well, then gently insert dispensing cap partway into the anus.
6. thoroughly cleanse dispensing cap after each use and replace cover
7. children under 12 years of age: ask a doctor

Inactive ingredients

aloe barbadensis leaf extract, butylated hydroxyanisole, carboxymethylcellulose sodium, cetyl alcohol, citric acid, edetate disodium, glyceryl monostearate, laureth-23, methylparaben, mineral oil, panthenol, propyl gallate, propylparaben, purified water, sodium benzoate, steareth-2, steareth-20, stearyl alcohol, vitamin E, xanthan gum

Questions or comments?

1-800-719-9260

Principal Display Panel

meijer®

MAXIMUM STRENGTH

Hemorrhoidal Cream

COMPARE TO PREPARATION H® CREAM ACTIVE INGREDIENTS

MULTI-SYMPTOM PAIN RELIEF SMOOTH CREAM FORMULA WITH ALOE & VITAMIN E

Rapid Soothing Relief From Painful Burning, Itching & Discomfort

Shrinks Swollen Hemorrhoidal Tissue

Protects Irritated Tissue

Relieves External Discomfort

NET WT. 1.8 OZ (51 g)